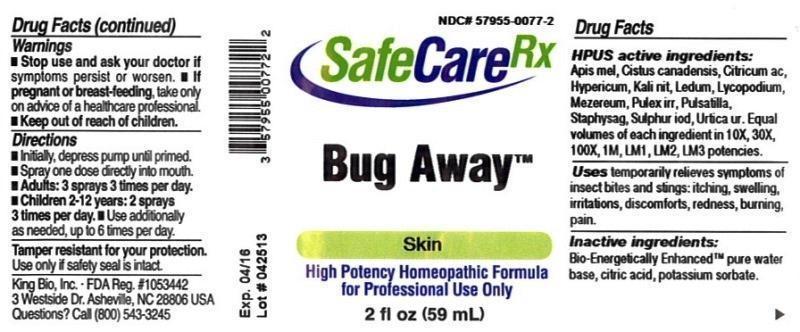 DRUG LABEL: Bug Away
NDC: 57955-0077 | Form: LIQUID
Manufacturer: King Bio Inc.
Category: homeopathic | Type: HUMAN OTC DRUG LABEL
Date: 20150306

ACTIVE INGREDIENTS: APIS MELLIFERA 10 [hp_X]/59 mL; HELIANTHEMUM CANADENSE 10 [hp_X]/59 mL; ANHYDROUS CITRIC ACID 10 [hp_X]/59 mL; HYPERICUM PERFORATUM 10 [hp_X]/59 mL; POTASSIUM NITRATE 10 [hp_X]/59 mL; LEDUM PALUSTRE TWIG 10 [hp_X]/59 mL; LYCOPODIUM CLAVATUM SPORE 10 [hp_X]/59 mL; DAPHNE MEZEREUM BARK 10 [hp_X]/59 mL; PULEX IRRITANS 10 [hp_X]/59 mL; PULSATILLA VULGARIS 10 [hp_X]/59 mL; DELPHINIUM STAPHISAGRIA SEED 10 [hp_X]/59 mL; SULFUR 10 [hp_X]/59 mL; URTICA URENS 10 [hp_X]/59 mL
INACTIVE INGREDIENTS: WATER; POTASSIUM SORBATE

Bug Away

ACTIVE INGREDIENT

Drug Facts__________________________________________________________________________________________________________

HPUS active ingredients: Apis mellifica, Cistus canadensis, Citricum acidum, Hypericum perforatum, Kali nitricum, Ledum palustre, Lycopodium clavatum, Mezereum, Pulex irritans, Pulsatilla, Staphysagria, Sulphur, Urtica Urens. Equal volumes of each ingredient in 10X, 30X, 100X, 1M, LM1, LM2, LM3 potencies.

INDICATIONS AND USAGE

Uses temporarily relieves symptoms of insect bites and stings: itching, swelling, irritations, discomforts, redness, burning pain.

Inactive Ingredients:

Bio-Energetically Enhanced™ pure water, citric acid and potassium sorbate.

Warnings

- Stop use and ask your doctor if symptoms persist or worsen.
- If pregnant or breast-feeding, take only on advice of a healthcare professional.

- Keep out of reach of children.

Directions

- Initially, depress pump until primed.
- Spray one dose directly into mouth.
- Adults: 3 sprays 3 times per day
- Children 2-12 years: 2 sprays 3 times per day.
- Use additionally as needed, up to 6 times per day.

OTHER SAFETY INFORMATION

Tamper resistant for your protection. Use only if safety seal is intact.

PURPOSE

Uses temporarily relieves symptoms of insect bites and stings:

- itching
- swelling
- irritations
- discomforts
- redness
- burning pain